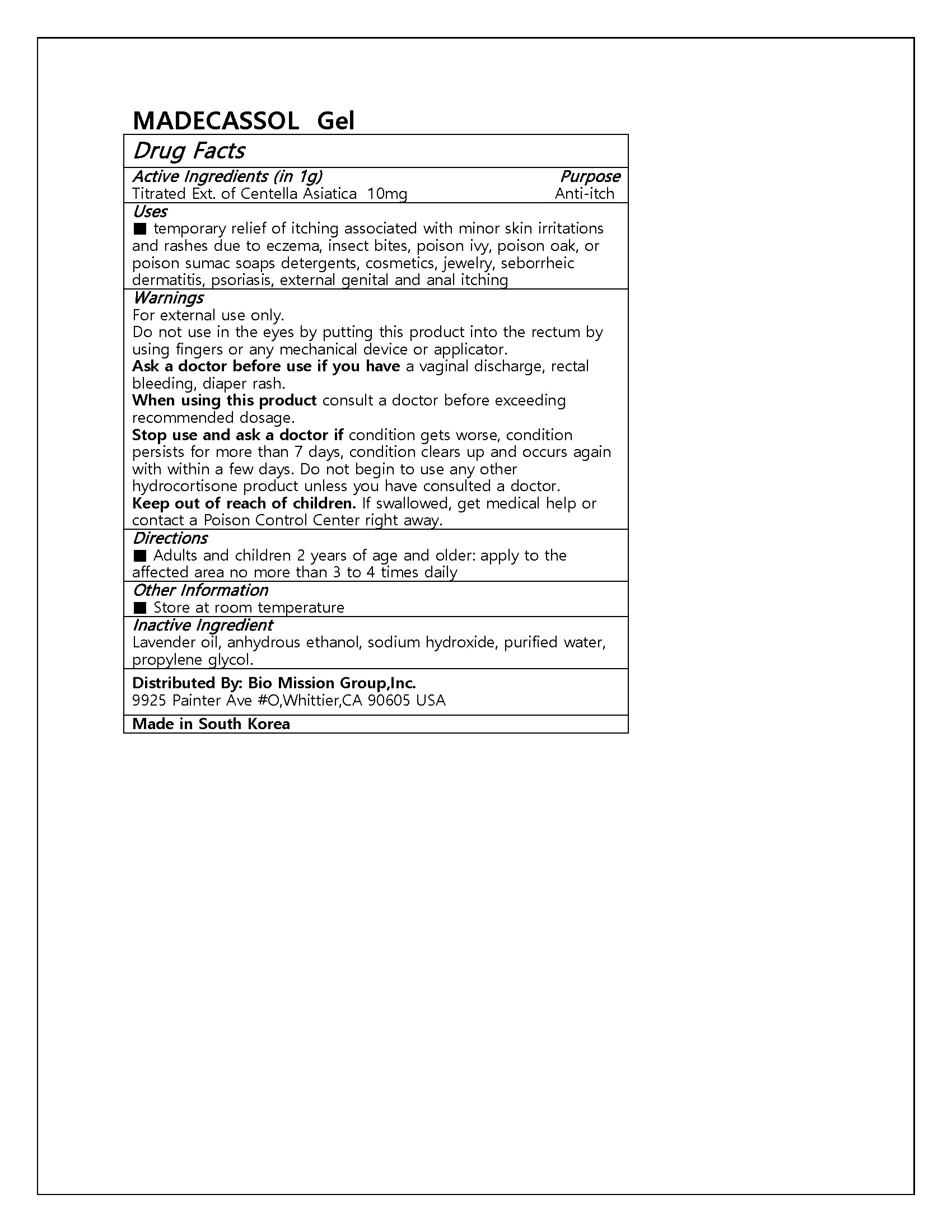 DRUG LABEL: MADECASSOL
NDC: 72988-0039 | Form: GEL
Manufacturer: Lydia Co., Ltd.
Category: otc | Type: HUMAN OTC DRUG LABEL
Date: 20240903

ACTIVE INGREDIENTS: CENTELLA ASIATICA 10 mg/1 g
INACTIVE INGREDIENTS: SODIUM HYDROXIDE

ACTIVE INGREDIENT

Titrated Ext. of Centella Asiatica

PURPOSE

temporary relief of itching associated with minor skin irritations and rashes due to eczema, insect bites, poison ivy, poison oak, or poison sumac soaps detergents, cosmetics, jewelry, seborrheic dermatitis, psoriasis, external genital and anal itching

Keep out of reach of children

INDICATIONS AND USAGE

Adults and children 2 years of age and older: apply to the affected area no more than 3 to 4 times daily

Warnings

For external use only.

Do not use in the eyes by putting this product into the rectum by using fingers or any mechanical device or applicator.

Ask a doctor before use if you have a vaginal discharge, rectal bleeding, diaper rash.

When using this product consult a doctor before exceeding recommended dosage.

Stop use and ask a doctor if condition gets worse, condition persists for more than 7 days, condition clears up and occurs again with within a few days. Do not begin to use any other hydrocortisone product unless you have consulted a doctor.

Keep out of reach of children. If swallowed, get medical help or contact a Poison Control Center right away.

INACTIVE INGREDIENT

Lavender oil, anhydrous ethanol, sodium hydroxide, purified water, propylene glycol.

DOSAGE AND ADMINISTRATION

for topical use